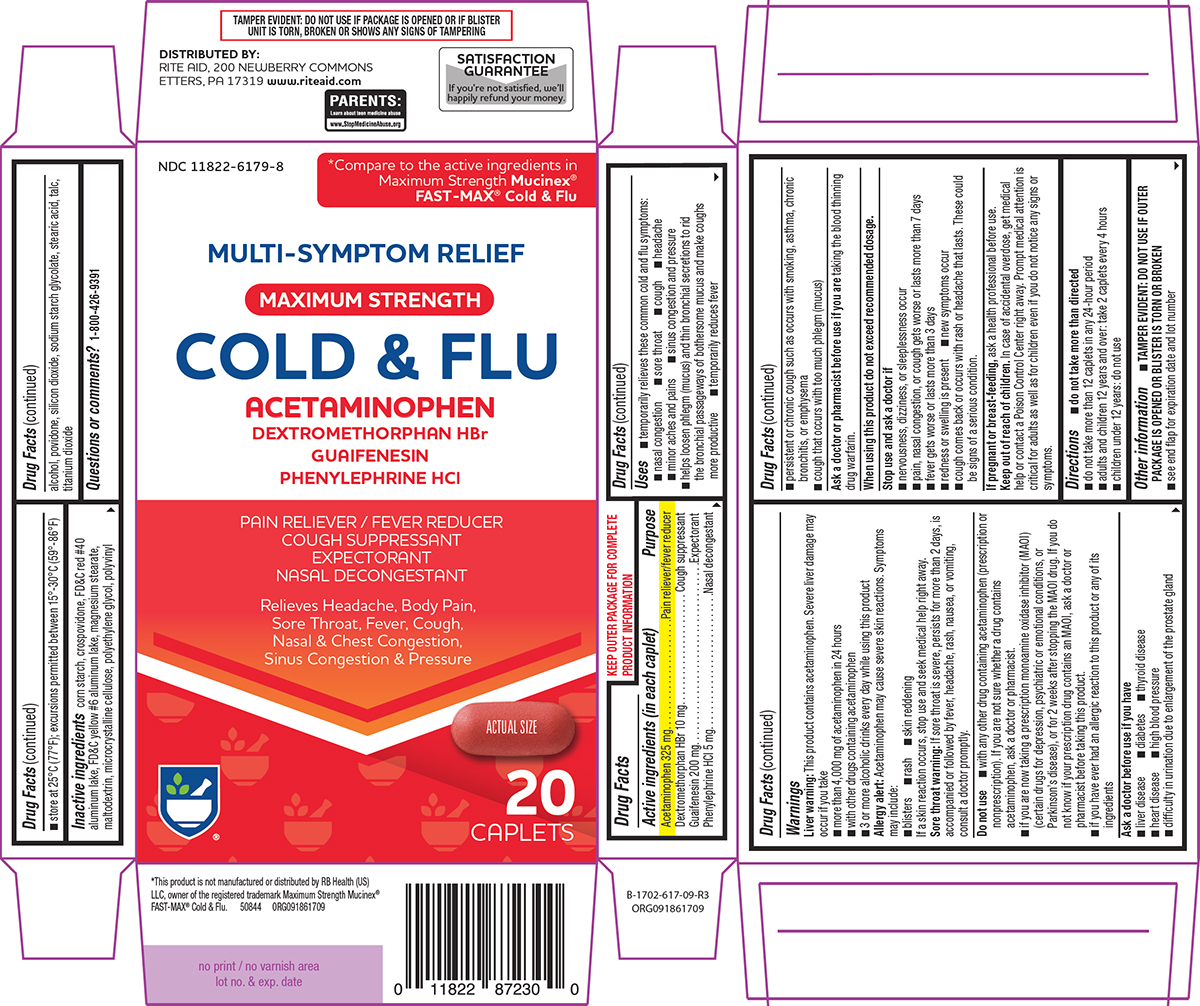 DRUG LABEL: Cold and Flu
NDC: 11822-6179 | Form: TABLET, FILM COATED
Manufacturer: Rite Aid Corporation
Category: otc | Type: HUMAN OTC DRUG LABEL
Date: 20251212

ACTIVE INGREDIENTS: ACETAMINOPHEN 325 mg/1 1; DEXTROMETHORPHAN HYDROBROMIDE 10 mg/1 1; GUAIFENESIN 200 mg/1 1; PHENYLEPHRINE HYDROCHLORIDE 5 mg/1 1
INACTIVE INGREDIENTS: STARCH, CORN; CROSPOVIDONE, UNSPECIFIED; FD&C RED NO. 40 ALUMINUM LAKE; FD&C YELLOW NO. 6 ALUMINUM LAKE; MAGNESIUM STEARATE; MALTODEXTRIN; MICROCRYSTALLINE CELLULOSE; POLYETHYLENE GLYCOL, UNSPECIFIED; POLYVINYL ALCOHOL, UNSPECIFIED; POVIDONE, UNSPECIFIED; SILICON DIOXIDE; SODIUM STARCH GLYCOLATE TYPE A POTATO; STEARIC ACID; TALC; TITANIUM DIOXIDE

Rite Aid 44-617 CF

Active ingredients (in each caplet)

Acetaminophen 325 mg
Dextromethorphan HBr 10 mg
Guaifenesin 200 mg
Phenylephrine HCl 5 mg

Purpose

Pain reliever/fever reducer
Cough suppressant
Expectorant
Nasal decongestant

Uses

- temporarily relieves these common cold and flu symptoms:
  - nasal congestion
  - sore throat
  - cough
  - headache
  - minor aches and pains
  - sinus congestion and pressure
- helps loosen phlegm (mucus) and thin bronchial secretions to rid the bronchial passageways of bothersome mucus and make coughs more productive
- temporarily reduces fever

Warnings

Liver warning: This product contains acetaminophen. Severe liver damage may occur if you take

- more than 4,000 mg of acetaminophen in 24 hours
- with other drugs containing acetaminophen
- 3 or more alcoholic drinks every day while using this product

Allergy alert: Acetaminophen may cause severe skin reactions. Symptoms may include:

- blisters
- rash
- skin reddening

If a skin reaction occurs, stop use and seek medical help right away.

Sore throat warning: If sore throat is severe, persists for more than 2 days, is accompanied or followed by fever, headache, rash, nausea, or vomiting, consult a doctor promptly.

Do not use

- with any other drug containing acetaminophen (prescription or nonprescription). If you are not sure whether a drug contains acetaminophen, ask a doctor or pharmacist.
- if you are now taking a prescription monoamine oxidase inhibitor (MAOI) (certain drugs for depression, psychiatric or emotional conditions, or Parkinson’s disease), or for 2 weeks after stopping the MAOI drug. If you do not know if your prescription drug contains an MAOI, ask a doctor or pharmacist before taking this product.
- if you have ever had an allergic reaction to this product or any of its ingredients

Ask a doctor before use if you have

- liver disease
- diabetes
- thyroid disease
- heart disease
- high blood pressure
- difficulty in urination due to enlargement of the prostate gland
- persistent or chronic cough such as occurs with smoking, asthma, chronic bronchitis, or emphysema
- cough that occurs with too much phlegm (mucus)

Ask a doctor or pharmacist before use if you are

taking the blood thinning drug warfarin.

When using this product

do not exceed recommended dosage.

Stop use and ask a doctor if

- nervousness, dizziness, or sleeplessness occur
- pain, nasal congestion, or cough gets worse or lasts more than 7 days
- redness or swelling is present
- fever gets worse or lasts more than 3 days
- new symptoms occur
- cough comes back or occurs with rash or headache that lasts. These could be signs of a serious condition.

If pregnant or breast-feeding,

ask a health professional before use.

Keep out of reach of children.

In case of accidental overdose, get medical help or contact a Poison Control Center right away. Prompt medical attention is critical for adults as well as for children even if you do not notice any signs or symptoms.

Directions

- do not take more than directed
- do not take more than 12 caplets in any 24-hour period
- adults and children 12 years and over: take 2 caplets every 4 hours
- children under 12 years: do not use

Other information

- TAMPER EVIDENT: DO NOT USE IF OUTER PACKAGE IS OPENED OR BLISTER IS TORN OR BROKEN
- see end flap for expiration date and lot number
- store at 25°C (77°F); excursions permitted between 15°-30°C (59°-86°F)

Inactive ingredients

corn starch, crospovidone, FD&C red #40 aluminum lake, FD&C yellow #6 aluminum lake, magnesium stearate, maltodextrin, microcrystalline cellulose, polyethylene glycol, polyvinyl alcohol, povidone, silicon dioxide, sodium starch glycolate, stearic acid, talc, titanium dioxide

Questions or comments?

1-800-426-9391

Principal display panel

NDC 11822-6179-8

*Compare to the active ingredients in
Maximum Strength Mucinex®
FAST-MAX® Cold & Flu

MULTI-SYMPTOM RELIEF

MAXIMUM STRENGTH

COLD & FLU
ACETAMINOPHEN
DEXTROMETHORPHAN HBr
GUAIFENESIN
PHENYLEPHRINE HCl

PAIN RELIEVER / FEVER REDUCER
COUGH SUPPRESSANT
EXPECTORANT
NASAL DECONGESTANT

Relieves Headache, Body Pain,
Sore Throat, Fever, Cough,
Nasal & Chest Congestion,
Sinus Congestion & Pressure

ACTUAL SIZE

20
CAPLETS

TAMPER EVIDENT: DO NOT USE IF PACKAGE IS OPENED OR IF BLISTER
UNIT IS TORN, BROKEN OR SHOWS ANY SIGNS OF TAMPERING

*This product is not manufactured or distributed by RB Health (US)
LLC, owner of the registered trademark Maximum Strength Mucinex®
FAST-MAX® Cold & Flu. 50844 ORG091861709

DISTRIBUTED BY:
RITE AID, 200 NEWBERRY COMMONS
ETTERS, PA 17319 www.riteaid.com

SATISFACTION
GUARANTEE
If you're not satisfied, we'll
happily refund your money.

PARENTS:
Learn about teen medicine abuse
www.StopMedicineAbuse.org

Rite Aid 44-617